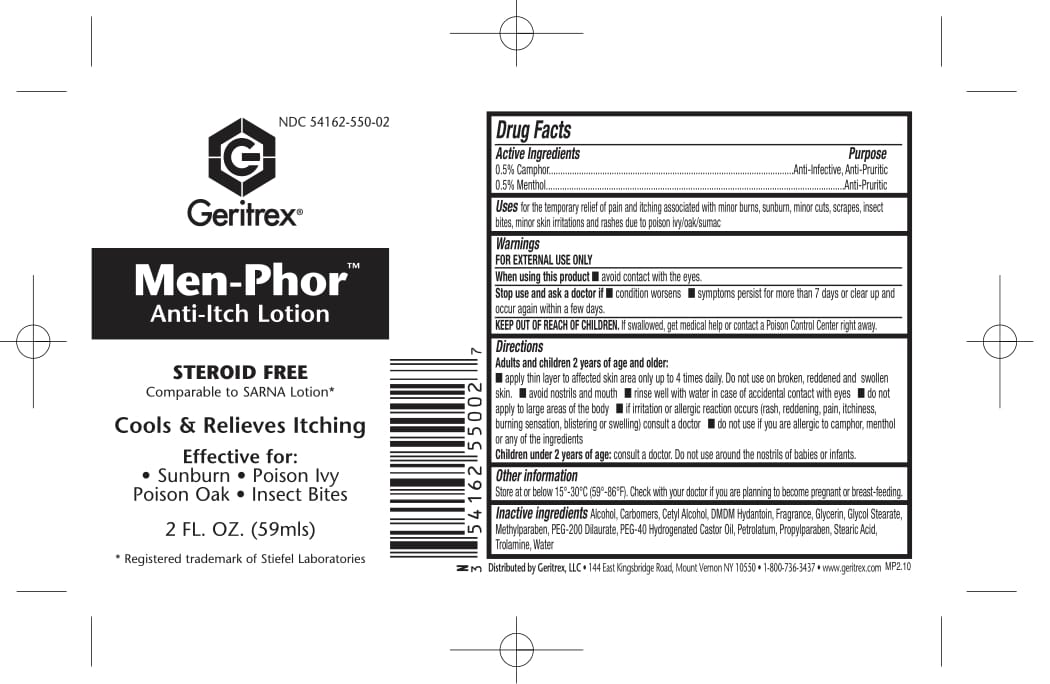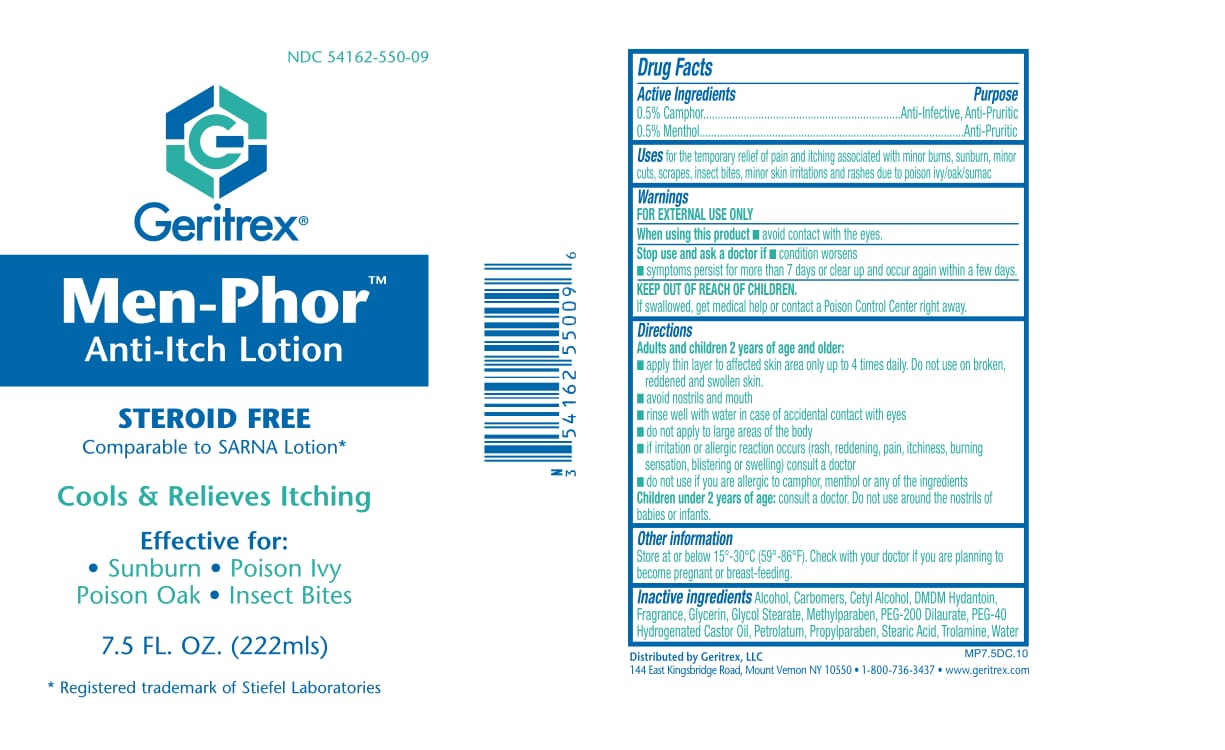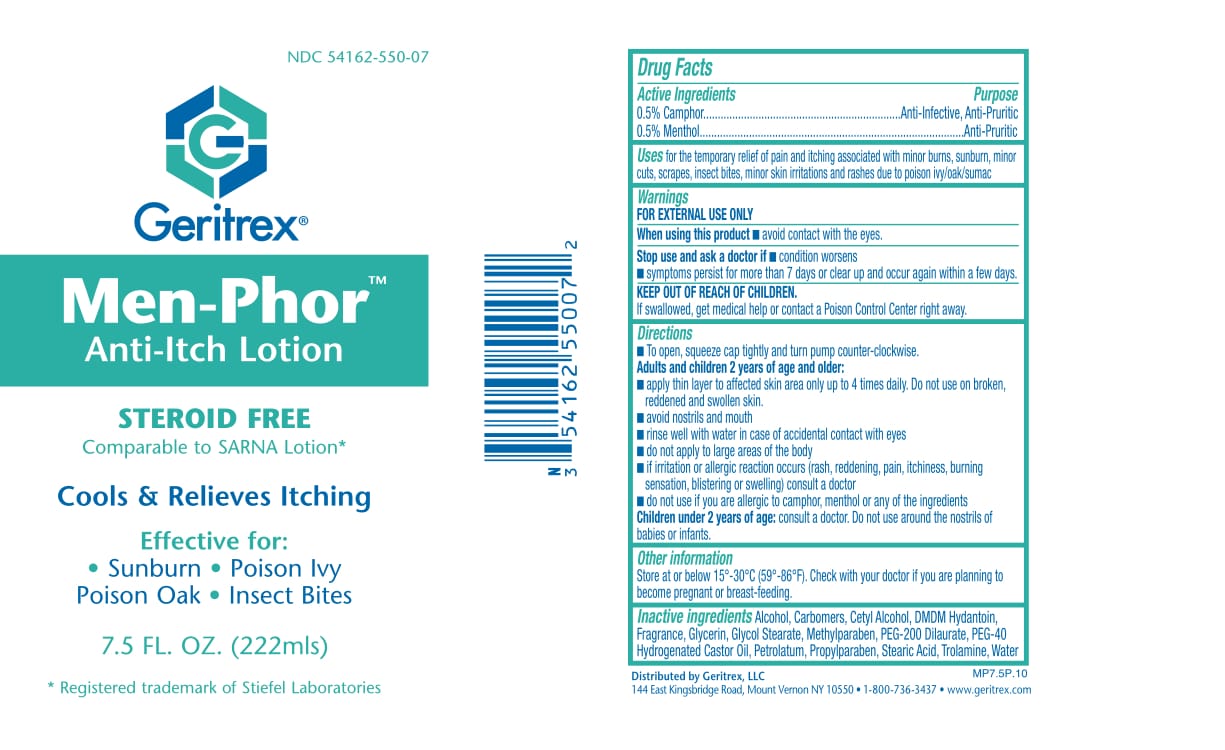 DRUG LABEL: Men-Phor
NDC: 54162-550 | Form: LOTION
Manufacturer: Geritrex LLC
Category: otc | Type: HUMAN OTC DRUG LABEL
Date: 20180117

ACTIVE INGREDIENTS: MENTHOL 1.11 g/222 mL; CAMPHOR (SYNTHETIC) 1.11 g/222 mL
INACTIVE INGREDIENTS: WATER; ALCOHOL; STEARIC ACID; CARBOMER HOMOPOLYMER TYPE C; CETYL ALCOHOL; DMDM HYDANTOIN; GLYCOL STEARATE; PEG-200 DILAURATE; PEG-40 CASTOR OIL; PETROLATUM; METHYLPARABEN; PROPYLPARABEN; TROLAMINE

Men-Phor

Drug Facts

Active Ingredients Purpose
0.5% Camphor . . . .Anti-Infective, Anti-Pruritic
0.5% Menthol . . . .Anti-Pruritic

Uses

To provide temporary relief for dry
itching skin, sunburn, insect bites and pruritus.

Directions

• Apply two or three times daily, or as directed
by your physician.

Warnings

For External Use Only
• Avoid contact with eyes. If contact occurs,
rinse eyes thoroughly with water.
• If improvement does not occur, or condition
worsens after regular use as directed,
discontinue use and consult a physician.
• Do not use on children under two years of age.
• Do not apply under compresses or bandages

Other Ingredient

Alcohol, Carbomers, Cetyl Alcohol, DMDM Hydantoin, Fragrance, Glycerin, Glycol Stearate, Methylparaben, PEG-200 Dilaurate, PEG-40 Hydrogenated Castor Oil, Petrolatum, Propylparaben, Stearic Acid, Trolamine, Water

Keep out of reach of children

DOSAGE AND ADMINISTRATION

Apply two or three times daily.